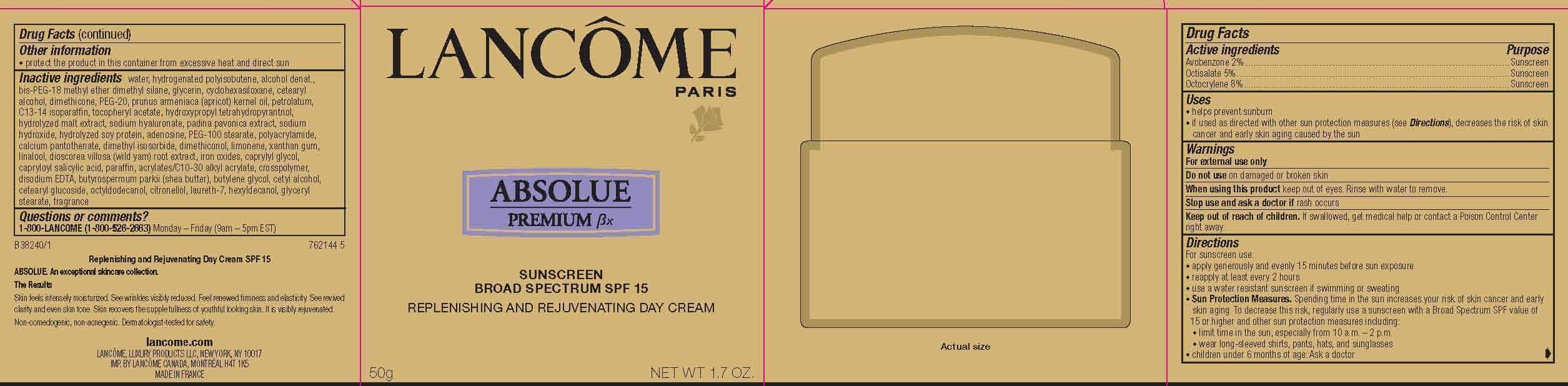 DRUG LABEL: Lancome Paris Absolue Premium Bx Replenishing Rejuvenating Broad Spectrum SPF 15 Day
NDC: 51150-953 | Form: CREAM
Manufacturer: SICOS ET CIE
Category: otc | Type: HUMAN OTC DRUG LABEL
Date: 20231223

ACTIVE INGREDIENTS: Avobenzone 20 mg/1 g; Octisalate 50 mg/1 g; Octocrylene 80 mg/1 g
INACTIVE INGREDIENTS: WATER; ALCOHOL; GLYCERYL STEARATE SE

Drug Facts

Active Ingredients

Avobenzone 2%

Octisalate 5%

Octocrylene 8%

Purpose

Sunscreen

Uses

- helps prevent sunburn

- if used as directed with other sun protection measures (see Directions), decreases the risk of skin cancer and early skin aging caused by the sun

Warnings

For external use only

Do not use

on damaged or broken skin

When using this product

keep out of eyes. Rinse with water to remove.

Stop use and ask a doctor if

rash occurs

Keep out of reach of children.

If swallowed, get medical help or contact a Poison Control Center right away.

Directions

For sunscreen use:

● apply generously and evenly 15 minutes before sun exposure

● reapply at least every 2 hours

● use a water resistant sunscreen if swimming or sweating

● Sun Protection Measures. Spending time in the sun increases your risk of skin cancer and early skin aging. To decrease this risk, regularly use a sunscreen with a Broad Spectrum SPF value of 15 or higher and other sun protection measures including:

● limit time in the sun, especially from 10 a.m. – 2 p.m.

● wear long-sleeved shirts, pants, hats, and sunglasses

● children under 6 months of age: Ask a doctor

Other information

protect the product in this container from excessive heat and direct sun

Inactive ingredients

water, hydrogenated polyisobutene, alcohol denat., bis-PEG-18 methyl ether dimethyl silane, glycerin, cyclohexasiloxane, cetearyl alcohol, dimethicone, PEG-20, prunus armeniaca (apricot) kernel oil, petrolatum, C13-14 isoparaffin, tocopheryl acetate, hydroxypropyl tetrahydropyrantriol, hydrolyzed malt extract, sodium hyaluronate, padina pavonica extract, sodium hydroxide, hydrolyzed soy protein, adenosine, PEG-100 stearate, polyacrylamide, calcium pantothenate, dimethyl isosorbide, dimethiconol, limonene, xanthan gum, linalool, dioscorea villosa (wild yam) root extract, iron oxides, caprylyl glycol, capryloyl salicylic acid, paraffin, acrylates/C10-30 alkyl acrylate, crosspolymer, disodium EDTA, butyrospermum parkii (shea butter), butylene glycol, cetyl alcohol, cetearyl glucoside, octyldodecanol, citronellol, laureth-7, hexyldecanol, glyceryl stearate, fragrance

Questions or comments?

1-800-LANCOME (1-800-526-2663) Monday - Friday (9 am - 5 pm EST)